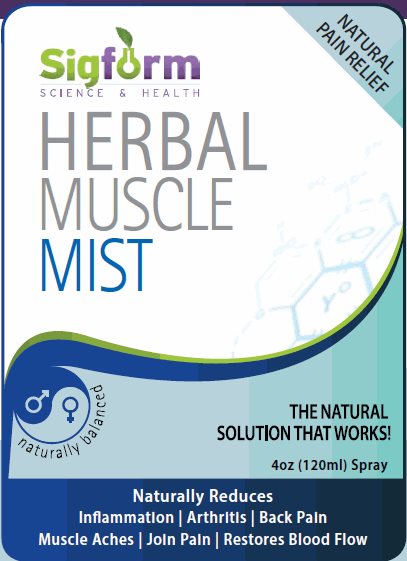 DRUG LABEL: Sigform Herbal Muscle Mist
NDC: 69257-210 | Form: SOLUTION
Manufacturer: Signature Formulations LLC
Category: otc | Type: HUMAN OTC DRUG LABEL
Date: 20150401

ACTIVE INGREDIENTS: MENTHOL 6 g/100 mL; CAMPHOR (SYNTHETIC) 2 g/100 mL
INACTIVE INGREDIENTS: ISOPROPYL ALCOHOL; DIMETHYL SULFONE; EUCALYPTUS OIL; METHYL SALICYLATE; PEPPERMINT OIL; CLOVE OIL

Sigform Science & Health Herbal Muscle Mist

Active ingredient

Menthol USP 6%
Camphor 2%

Purpose

Pain Relief

Other ingredients

Isopropyl Alcohol, MSM (Methylsulfonylmethane), Eucalytus Globulus Leaf Oil, Sweet Birch Oil, Peppermint Oil, Clove Bud Oil, Arnica Oil.

Uses

For the temporary relief of minor aches and pains at muscles and joints associated with sore muscles, strains, joint discomfort, and arthritis.

Warnings

For external use only. Avoid contact with eyes. Do not apply to wounds or damaged skin. If pregnant or breast feeding ask a health care professional before use. Flammable: Keep away from fire or flame.

Keep Out of Reach of Children

If swallowed get medical help or cantact a poison control center.

Directions

Adults and children over 12 years. Spray onto neck and shoulders to help relieve tension and stress. Rub into temples to help with headaches. Spray onto chest to relieve cold and flu. Apply prior to a workout or sports activity.

Manufactured in a FDA facility Exclusively for

Sigform LLC
Tempe, Arizona

Package/Label Principal Display Panel

Sigform
SCIENCE & HEALTH

NATURAL PAIN RELIEF

HERBAL
MUSCLE
MIST

naturally balanced

THE NATURAL SOLUTION THAT WORKS!

4oz (120ml) Spray

Naturally Reduces
Inflammation | Arthritis | Back Pain
Muscle Aches | Join Pain | Restores Blood Flow

Carton Label